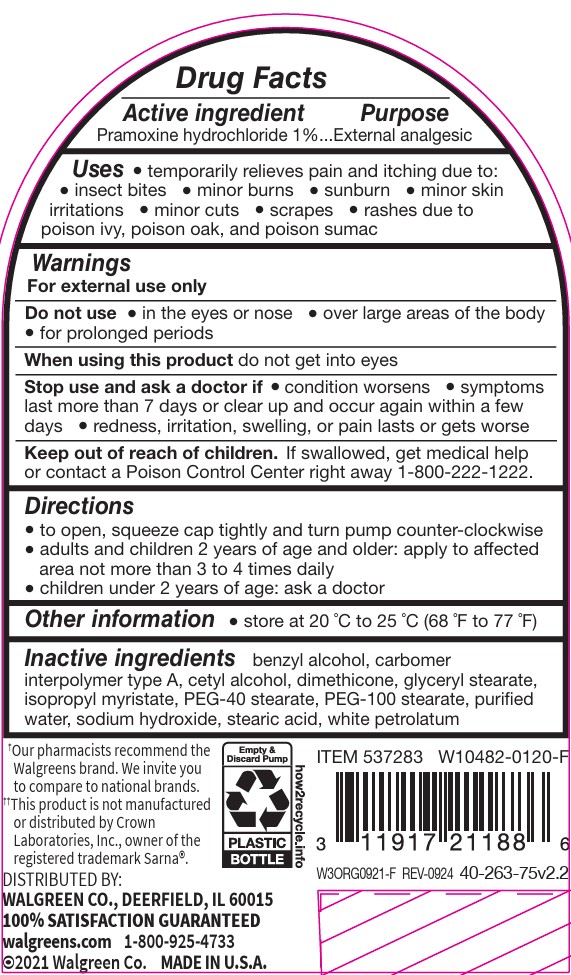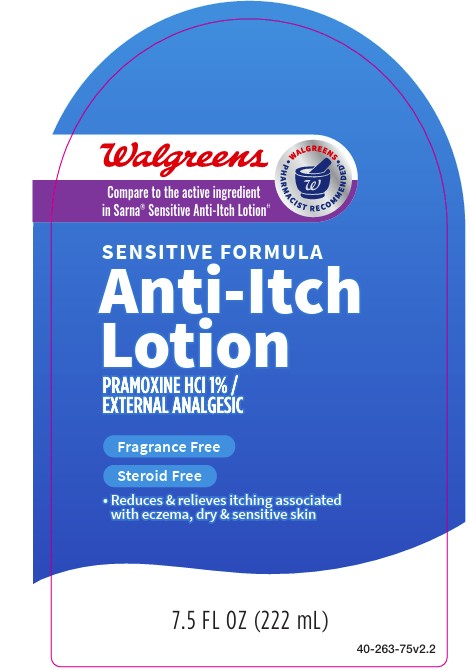 DRUG LABEL: Walgreen Anti-Itch
NDC: 0363-0263 | Form: LOTION
Manufacturer: Walgreens
Category: otc | Type: HUMAN OTC DRUG LABEL
Date: 20251119

ACTIVE INGREDIENTS: PRAMOXINE HYDROCHLORIDE 1 g/100 g
INACTIVE INGREDIENTS: BENZYL ALCOHOL; ISOPROPYL MYRISTATE; STEARIC ACID; GLYCERYL STEARATE/PEG-100 STEARATE; SODIUM HYDROXIDE; WATER; DIMETHICONE 350; PEG-40 STEARATE; CARBOMER INTERPOLYMER TYPE A (55000 CPS); PETROLATUM

Walgreen Sensitive Anti-Itch Lotion

ACTIVE INGREDIENT

Pramoxine HCl 1%

Uses

temporary relieves pain and itching due to:

insect bites

minor burns

sunburn

minor skin irritations

minor cuts

scrapes

rashes due to poison ivy, poison oak, and poison sumac

dries the oozing and weeping of poison:

ivy

oak

sumac

Warning

For external use only

Do not use

in the eyes or nose

over large areas of the body for prolonged periods

Ask doctor before use

on chicken pox

on measles

When using this product

do not get into eyes

Stop Use and ask doctor if

condition worsens

symptoms last more than 7 days or clear up and occur again within a few days

Keep out of reach of children

If swallowed, get medical help or contact a Poison Control Center right away.

Purpose

Anti-Itch

External Analgesic

Directions

to open, squeeze cap tightly and turn pump counter-clockwise

adults and children 2 years and older: apply to affected area not more than 3 to 4 times daily

children under 2 years: ask a doctor

Other information

store at 20 °C to 25 °C (68 °F to 77 °F)

INACTIVE INGREDIENT

benzyl alcohol, carbomer interpolymer type A, cetyl alcohol, dimethicone, glyceryl stearate, isopropyl myristate, PEG-40 stearate,
PEG-100 stearate, purified water, sodium hydroxide, stearic acid, white petrolatum

PACKAGE LABEL

Walgreens

Compare to Sarna Sensitive Anti-Itch Lotion

Sensitive Formula Anti-Itch Lotion

Pramoxine Hydrochloride 1 percent

Steroid Free

Reduces and Relieves Itching associated with eczema, dry and sensitive skin